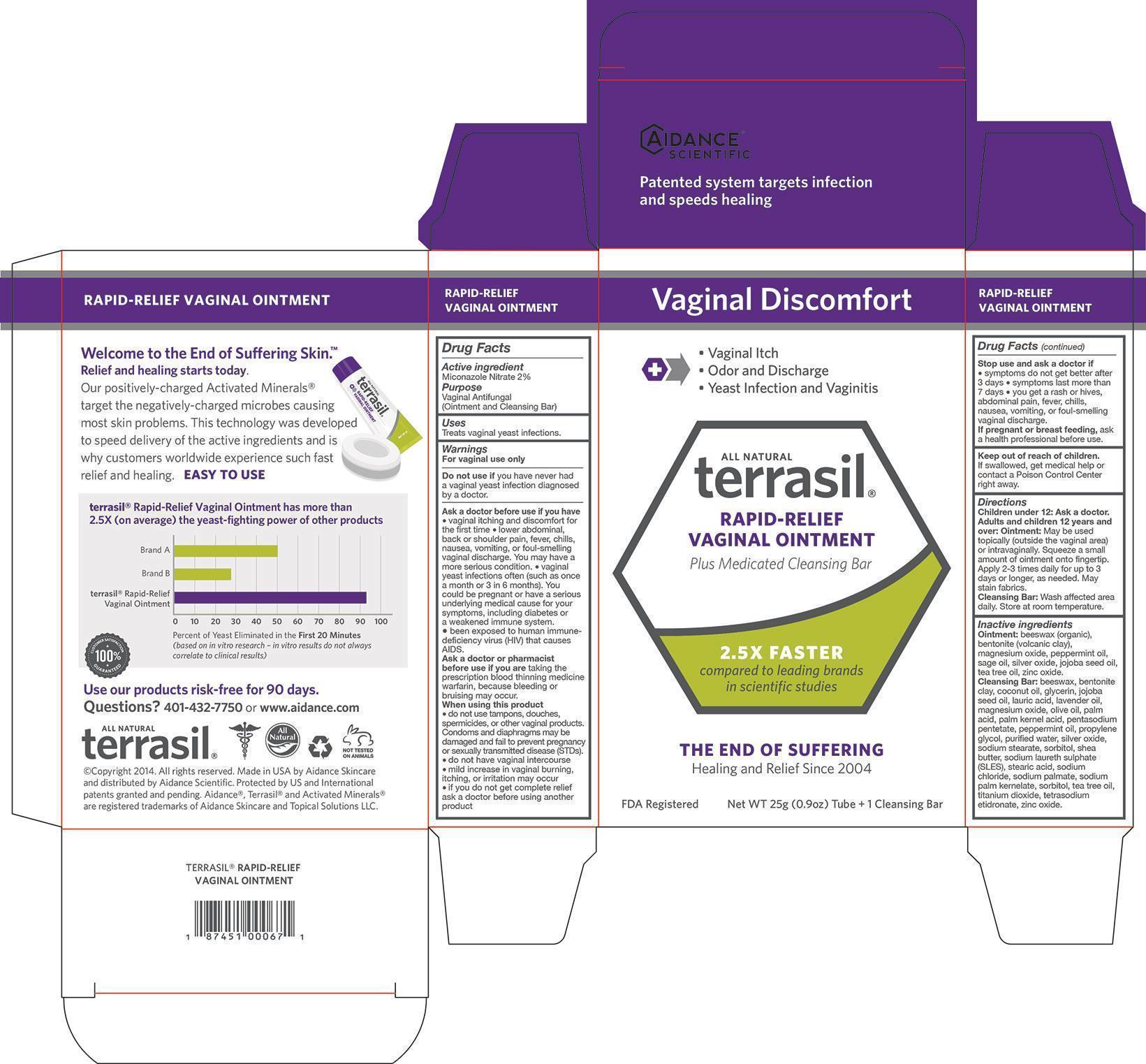 DRUG LABEL: Terrasil Rapid-Relief Vaginal
NDC: 24909-162 | Form: KIT | Route: TOPICAL
Manufacturer: Aidance Skincare & Topical Solutions, LLC
Category: otc | Type: HUMAN OTC DRUG LABEL
Date: 20140418

ACTIVE INGREDIENTS: MICONAZOLE NITRATE 2 g/100 g; MICONAZOLE NITRATE 2 g/100 g
INACTIVE INGREDIENTS: BENTONITE; JOJOBA OIL; MAGNESIUM OXIDE; PEPPERMINT OIL; SAGE OIL; SILVER OXIDE; TEA TREE OIL; WHITE WAX; ZINC OXIDE; BENTONITE; COCONUT OIL; GLYCERIN; JOJOBA OIL; LAURIC ACID; LAVENDER OIL; MAGNESIUM OXIDE; OLIVE OIL; PALM ACID; PALM KERNEL ACID; PENTASODIUM PENTETATE; PEPPERMINT OIL; PROPYLENE GLYCOL; SILVER OXIDE; SODIUM STEARATE; SHEA BUTTER; SODIUM LAURETH SULFATE; STEARIC ACID; SODIUM CHLORIDE; SODIUM PALMATE; SODIUM PALM KERNELATE; SORBITOL; TEA TREE OIL; TITANIUM DIOXIDE; ETIDRONATE TETRASODIUM; WATER; WHITE WAX; ZINC OXIDE

Drug Facts

Active Ingredient

Miconazole Nitrate 2%

Purpose

Vaginal Antifungal

Uses

Treats vaginal yeast infections.

Warnings

For vaginal use only

Do not use if you have never had a vaginal yeast infection diagnosed by a doctor.

Ask a doctor before use if you have
● vaginal itching and discomfort for the first time
● lower abdominal, back or shoulder pain, fever, chills, nausea, vomiting, or foul-smelling
vaginal discharge. You may have a more serious condition.
● vaginal yeast infections often (such as once a month or 3 in 6 months).
You could be pregnant or have a serious underlying medical cause for your
symptoms, including diabetes or a weakened immune system.
● been exposed to human immunedeficiency virus (HIV) that causes AIDS.

Ask a doctor or pharmacist before use if you are taking the prescription blood thinning medicine
warfarin, because bleeding or bruising may occur.

When using this product
● do not use tampons, douches, spermicides, or other vaginal products.
Condoms and diaphragms may be damaged and fail to prevent pregnancy
or sexually transmitted disease (STDs).
● do not have vaginal intercourse
● mild increase in vaginal burning, itching, or irritation may occur
● if you do not get complete relief ask a doctor before using another product

Stop use and ask a doctor if
● symptoms do not get better after 3 days
● symptoms last more than 7 days
● you get a rash or hives, abdominal pain, fever, chills, nausea, vomiting, or foul-smelling vaginal discharge.
If pregnant or breast feeding, ask a health professional before use.

Keep out of reach of children.

If swallowed, get medical help or contact a Poison Control Center right away.

Directions

Children under 12: Ask a doctor.
Adults and children 12 years and over:
Ointment: May be used topically (outside the vaginal area) or intravaginally.
Squeeze a small amount of ointment onto fingertip.
Apply 2-3 times daily for up to 3 days or longer, as needed. May stain fabrics.
Cleansing Bar: Wash affected areadaily. Store at room temperature.

Inactive Ingredients

Ointment: beeswax (organic), bentonite (volcanic clay), jojoba seed oil, magnesium oxide, peppermint oil, sage oil, silver oxide, tea tree oil, zinc oxide.

Cleansing Bar: beeswax, bentonite clay, coconut oil, glycerin, jojoba seed oil, lauric acid, lavender oil, magnesium oxide, olive oil, palm acid, palm kernel acid, pentasodium pentetate, peppermint oil, propylene glycol, purified water, silver oxide, sodium stearate, sorbitol, shea butter, sodium laureth sulphate (SLES), stearic acid, sodium chloride, sodium palmate, sodium palm kernelate, sorbitol, tea tree oil, titanium dioxide, tetrasodium etidronate, zinc oxide.

PRINCIPAL DISPLAY PANEL - BOX

Vaginal Discomfort

- Vaginal Itch
- Odor and Discharge
- Yeast Infection and Vaginitis

All Natural

terrasil

RAPID-RELIEF VAGINAL OINTMENT

Plus Medicated Cleansing Bar

2.5X FASTER

compared to leading brands
in scientific studies

THE END OF SUFFERING

Healing and Relief Since 2004